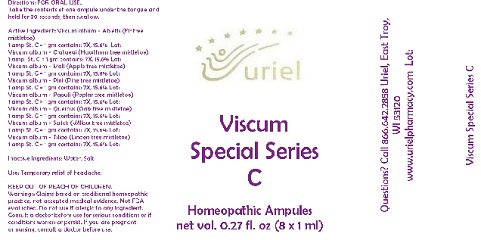 DRUG LABEL: Viscum Special Series C
NDC: 48951-9330 | Form: LIQUID
Manufacturer: Uriel Pharmacy Inc.
Category: homeopathic | Type: HUMAN OTC DRUG LABEL
Date: 20180516

ACTIVE INGREDIENTS: VISCUM ALBUM FRUITING TOP 7 [hp_X]/1 mL
INACTIVE INGREDIENTS: WATER; SODIUM CHLORIDE

Viscum Special Series C

INDICATIONS AND USAGE

Directions: FOR ORAL USE.

DOSAGE AND ADMINISTRATION

Take the contents of one ampule under the tongue and hold for 30 seconds, then swallow.

Active Ingredient: Viscum album - Abietis (Fir tree mistletoe)
1 amp St. C = 1 gm contains: 7X, 15.6%
Viscum album - Crataegi (Hawthorn tree mistletoe)
1 amp St. C = 1 gm contains: 7X, 15.6%
Viscum album - Mali (Apple tree mistletoe)
1 amp St. C = 1 gm contains: 7X, 15.6%
Viscum album - Pini (Pine tree mistletoe)
1 amp St. C = 1 gm contains: 7X, 15.6%
Viscum album - Populi (Poplar tree mistletoe)
1 amp St. C = 1 gm contains: 7X, 15.6%
Viscum album - Quercus (Oak tree mistletoe)
1 amp St. C = 1 gm contains: 7X, 15.6%
Viscum album - Salicis (Willow tree mistletoe)
1 amp St. C = 1 gm contains: 7X, 15.6%
Viscum album - Tiliae (Linden tree mistletoe)
1 amp St. C = 1 gm contains: 7X, 15.6%

Inactive Ingredients: Water, Salt

PURPOSE

Use: Temporary relief of headache.

KEEP OUT OF REACH OF CHILDREN.

WARNINGS

Warnings: Claims based on traditional homeopathic practice, not accepted medical evidence. Not FDA evaluated. Do not use if allergic to any ingredient. Consult a doctor before use for serious conditions or if conditions worsen or persist. If you are pregnant
or nursing, consult a doctor before use.

QUESTIONS

Questions? Call 866.642.2858 Uriel, East Troy, WI 53120
www.urielpharmacy.com